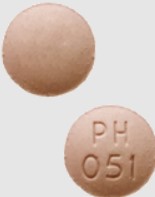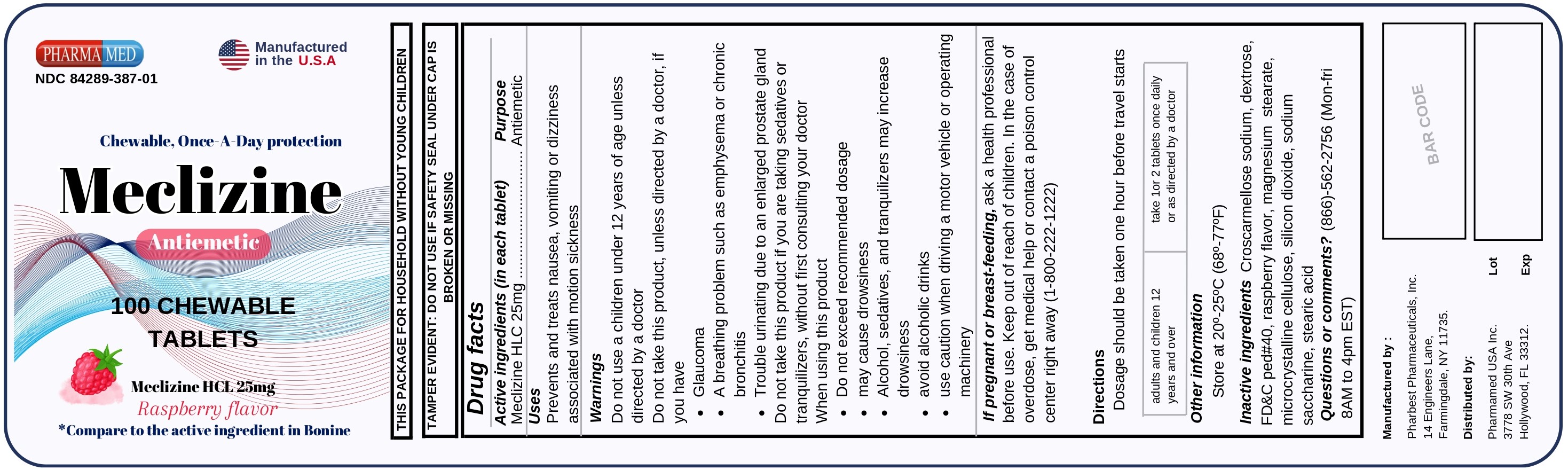 DRUG LABEL: Meclizine
NDC: 84289-387 | Form: TABLET, CHEWABLE
Manufacturer: PHARMAMED USA INC
Category: otc | Type: HUMAN OTC DRUG LABEL
Date: 20240626

ACTIVE INGREDIENTS: MECLIZINE HYDROCHLORIDE 25 mg/1 1
INACTIVE INGREDIENTS: CELLULOSE, MICROCRYSTALLINE; SILICON DIOXIDE; DEXTROSE; STEARIC ACID; MAGNESIUM STEARATE; CROSCARMELLOSE SODIUM; SACCHARIN SODIUM; FD&C RED NO. 40; RASPBERRY

Meclizine HCL 25mg

Active ingredient (in each tablet)

Meclizine HCl 25mg

Purpose

Antiemetic

Uses

prevents and treats nausea, vomiting or dizziness associated with motion sickness

Warnings

Do not use in children under 12 years of age unless directed by a doctor.

Do not take this product unless directed by a doctor if you have

- glaucoma
- a breathing problem such as emphysema or chronic bronchitis
- trouble urinating due to an enlarged prostate gland

Do not take this product if you are taking sedatives or tranquilizers, without first consulting your doctor.

When using this product

- do not exceed the recommended dosage
- may cause drowsiness
- alcohol, sedatives, and tranquilizers may increase drowsiness
- avoid alcoholic drinks
- use caution when driving a motor vehicle or operating machinery

If pregnant or breast-feeding,

ask a health professional before use.

Keep out of reach of children.

In case of overdose, get medical help or contact a Poison Control Center right away (1 800-222-1222)

Directions

- dosage should be taken one hour before travel starts

Adults and children 12 years and over | take 1 or 2 tablets once daily or as directed by doctor

Other information

- Tamper Evident: do not use if the safety seal under cap is broken or missing
- store at 20°-25°C (68°-77°F)

Inactive ingredients

Croscarmellose sodium, dextrose, FD&C Red#40, raspberry flavor, magnesium stearate, microcrystalline cellulose, silicon dioxide, sodium saccharine, stearic acid

Questions or comments?

(866) 562-2756 (Mon - Fri, 8AM - 4PM EST)

Package Label Principal Display Panel

PHARMAMED

NDC 84289-387-01

Manufactured in the USA

Chewable, Once-A-Day Protection

MECLIZINE

Antiemetic

100 CHEWABLE TABLETS

Meclizine HCL 25mg

Raspberry Flavor

*Compare to the active ingredient in Bonine